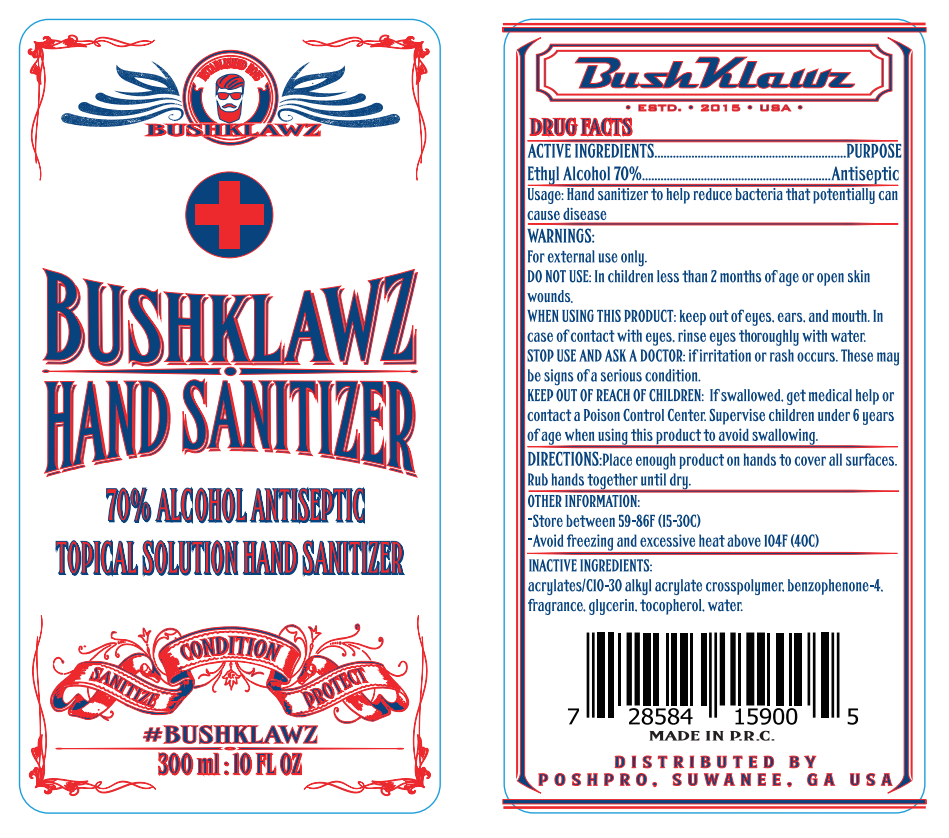 DRUG LABEL: Hand Sanitizer
NDC: 92284-002 | Form: GEL
Manufacturer: Poshpro LLC
Category: otc | Type: HUMAN OTC DRUG LABEL
Date: 20200814

ACTIVE INGREDIENTS: ALCOHOL 210 mL/300 mL
INACTIVE INGREDIENTS: GLYCERIN; WATER; CARBOMER INTERPOLYMER TYPE A (55000 CPS); TOCOPHEROL

DOSAGE AND ADMINISTRATION

1.Store between 59-86°F (15-30°C)
2.Avoid freezing and excessive heat above 104°F (40°C)

INACTIVE INGREDIENT

Aqua, Glycerin, Acrylates/C10-30 Alkyl Acrylate Cross Polymer, Tocopherol

INDICATIONS AND USAGE

Place enough product on hands to cover all surfaces.Rub hands together until dry.

ACTIVE INGREDIENT

Ethyl Alcohol

DO NOT USE

In children less than 2 months of age or open skin wounds.

keep out of reach of children

PURPOSE

Disinfection
Sterilization
No Rinseing

WARNINGS

For external use only.